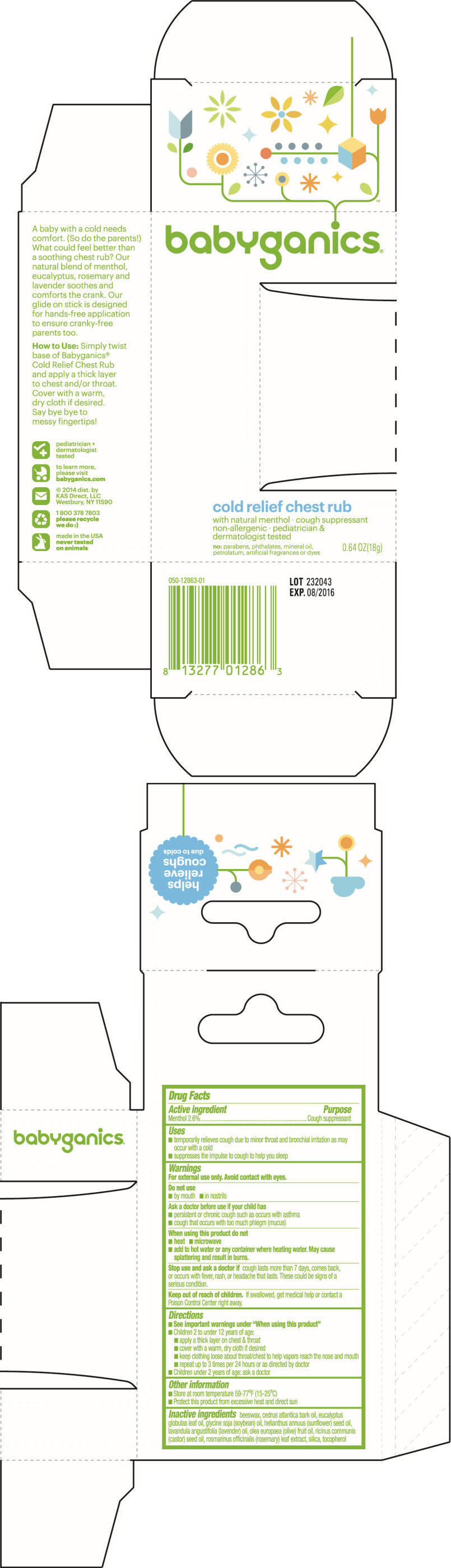 DRUG LABEL: BabyGanics Cold Relief Chest Rub
NDC: 59062-1286 | Form: STICK
Manufacturer: KAS Direct LLC dba BabyGanics
Category: otc | Type: HUMAN OTC DRUG LABEL
Date: 20180123

ACTIVE INGREDIENTS: MENTHOL, UNSPECIFIED FORM 2.6 mg/1 g
INACTIVE INGREDIENTS: YELLOW WAX; CEDRUS ATLANTICA BARK OIL; EUCALYPTUS OIL; SOYBEAN OIL; SUNFLOWER OIL; LAVENDER OIL; OLIVE OIL; CASTOR OIL; ROSEMARY; SILICON DIOXIDE; TOCOPHEROL

BabyGanics® Cold Relief Chest Rub

Drug Facts

Active ingredient

Menthol 2.6%

Purpose

Cough suppressant

Uses

- temporarily relieves cough due to minor throat and bronchial irritation as may occur with a cold
- suppresses the impulse to cough to help you sleep

Warnings

For external use only. Avoid contact with eyes.

Do not use

- by mouth
- in nostrils

Ask a doctor before use if your child has

- persistent or chronic cough such as occurs with asthma
- cough that occurs with too much phlegm (mucus)

When using this product do not

- heat
- microwave
- add to hot water or any container where heating water. May cause splattering and result in burns.

Stop use and ask a doctor if cough lasts more than 7 days, comes back, or occurs with fever, rash, or headache that lasts. These could be signs of a serious condition.

Keep out of reach of children. If swallowed, get medical help or contact a Poison Control Center right away.

Directions

- see important warnings under "When using this product"
- children 2 to under 12 years of age:
  - apply a thick layer on chest & throat
  - cover with a warm, dry cloth if desired
  - keep clothing loose about throat/chest to help vapors reach the nose and mouth
  - repeat up to 3 times per 24 hours or as directed by doctor
- children under 2 years of age: ask a doctor

Other information

- store at room temperature 59-77°F (15-25°C)
- protect this product from excessive heat and direct sun

Inactive ingredients

beeswax, cedrus atlantica bark oil, eucalyptus globulas leaf oil, glycine soja (soybean) oil, helianthus annuus (sunflower) seed oil, lavandula angustifolia (lavender) oil, olea europaea (olive) fruit oil, ricinus communis (castor) seed oil, rosmarinus officinalis (rosemary) leaf extract, silica, tocopherol

Dist. by:
KAS Direct, LLC.
Hicksville, NY 11801

PRINCIPAL DISPLAY PANEL - 18 g Tube Box

babyganics®

cold relief chest rub

with natural menthol ∙ cough suppressant
non-allergenic ∙ pediatrician &
dermatologist tested

no: parabens, phthalates, mineral oil,
petrolatum, artificial fragrances or dyes

0.64 OZ(18g)